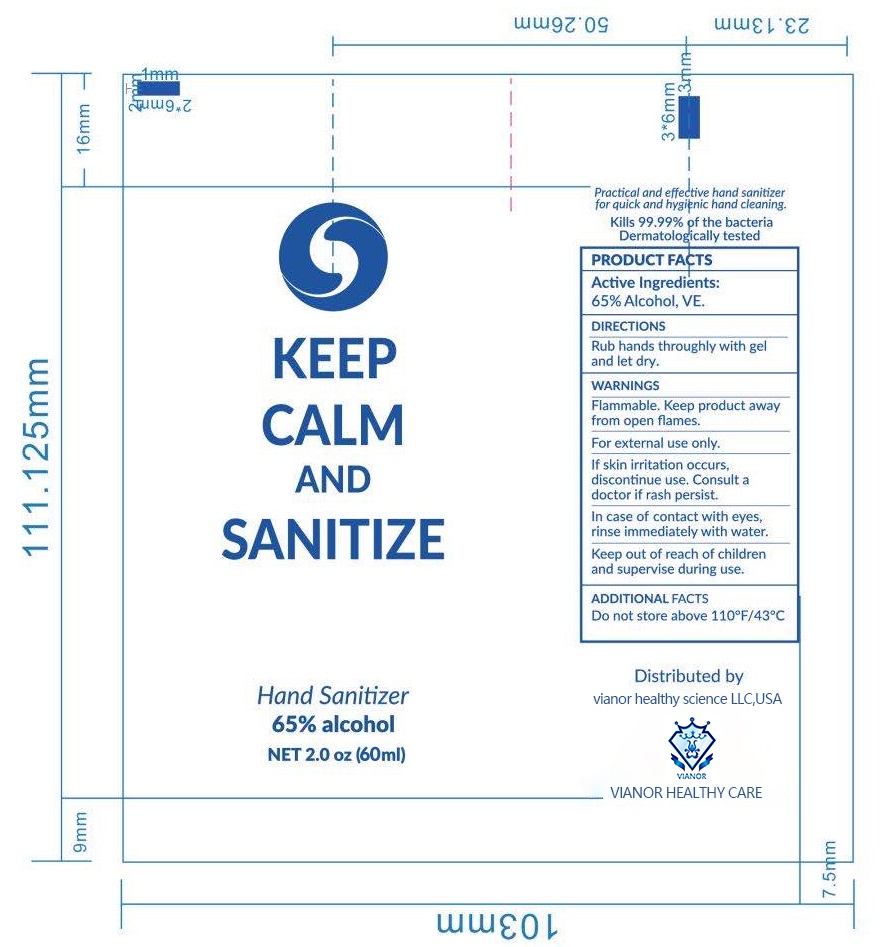 DRUG LABEL: Hand Sanitizer
NDC: 69980-101 | Form: GEL
Manufacturer: Shandong Vianor Healthy Science Co., Ltd.
Category: otc | Type: HUMAN OTC DRUG LABEL
Date: 20200521

ACTIVE INGREDIENTS: ALCOHOL 39 mL/60 mL
INACTIVE INGREDIENTS: WATER; .ALPHA.-TOCOPHEROL, D-

Vianor, Hand Sanitizer, 65% Alcohol, Gel, 60mL

Active Ingredient(s)

Alcohol 65% v/v. Purpose: Antimicrobial

Purpose

Antimicrobial

Use

Hand sanitizer to help reduce bacteria on the skin.

Warnings

Flammable. Keep product away from open flames.

For external use only.

Do not use on children less than 2 months of age.

Do not use on open skin wounds.

When using this product, avoid contact with eyes and broken skin.

In case of contact with eyes, rinse immediately with water.

STOP USE

If skin irritation occurs, discontinue use. Consult a doctor if rash persit.

Keep out of reach of children and superise during use.

Directions

Rua hands throughly with gel and let dry.

Other information

Do not strore above 110℉/43℃.

Inactive ingredients

Water, VE.